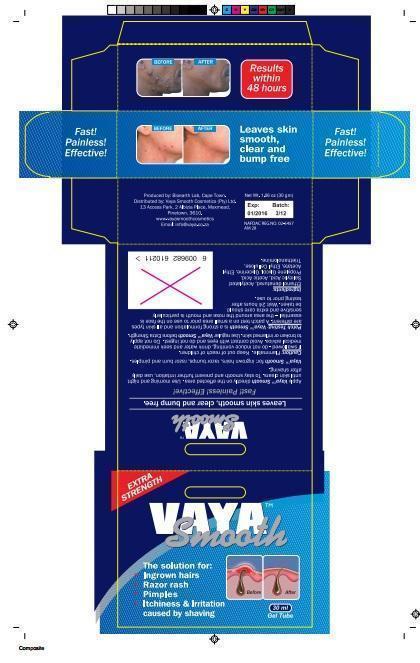 DRUG LABEL: Vaya Smooth Male
NDC: 62955
Manufacturer: Vaya Smooth Cosmetics (Pty) Ltd
Category: other | Type: COSMETIC
Date: 20151019

Vaya Smooth Aftershave

Vaya Smooth packaging label Male-30ml.jpg